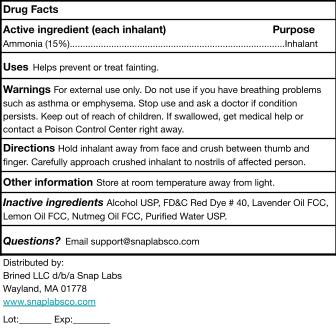 DRUG LABEL: Snap Labs Ammonia Inhalants
NDC: 87270-003 | Form: INHALANT
Manufacturer: Brined LLC d/b/a Snap Labs
Category: otc | Type: HUMAN OTC DRUG LABEL
Date: 20260130

ACTIVE INGREDIENTS: AMMONIA 150 mg/1 mL
INACTIVE INGREDIENTS: LEMON OIL; ALCOHOL; FD&C RED NO. 40; LAVENDER OIL; WATER; NUTMEG OIL

87270-003-02

Active Ingredients

Ammonia (15%)...Inhalant

Uses

Helps prevent or treat fainting.

Warnings

For external use only. Do not use if you have breathing problems such as asthma or emphysema. Stop use and ask a doctor if condition persists. Keep out of reach of children. If swallowed, ge

medical help or contact a Poison Control Center right away.

Keep out of reach of children

Do not use if you have breathing problems such as asthma or emphysema.

Inactive Ingredients

Inactive ingredients Alcohol USP, FD&C Red Dye # 40, Lavender Oil FCC, Lemon Oil FCC, Nutmeg Oil FCC, Purified Water USP.

Dosage and Administration

Hold inhalant away from face and crush between thumb and finger. Carefully approach crushed inhalant to nostrils of affected person.

Purpose

Inhalant